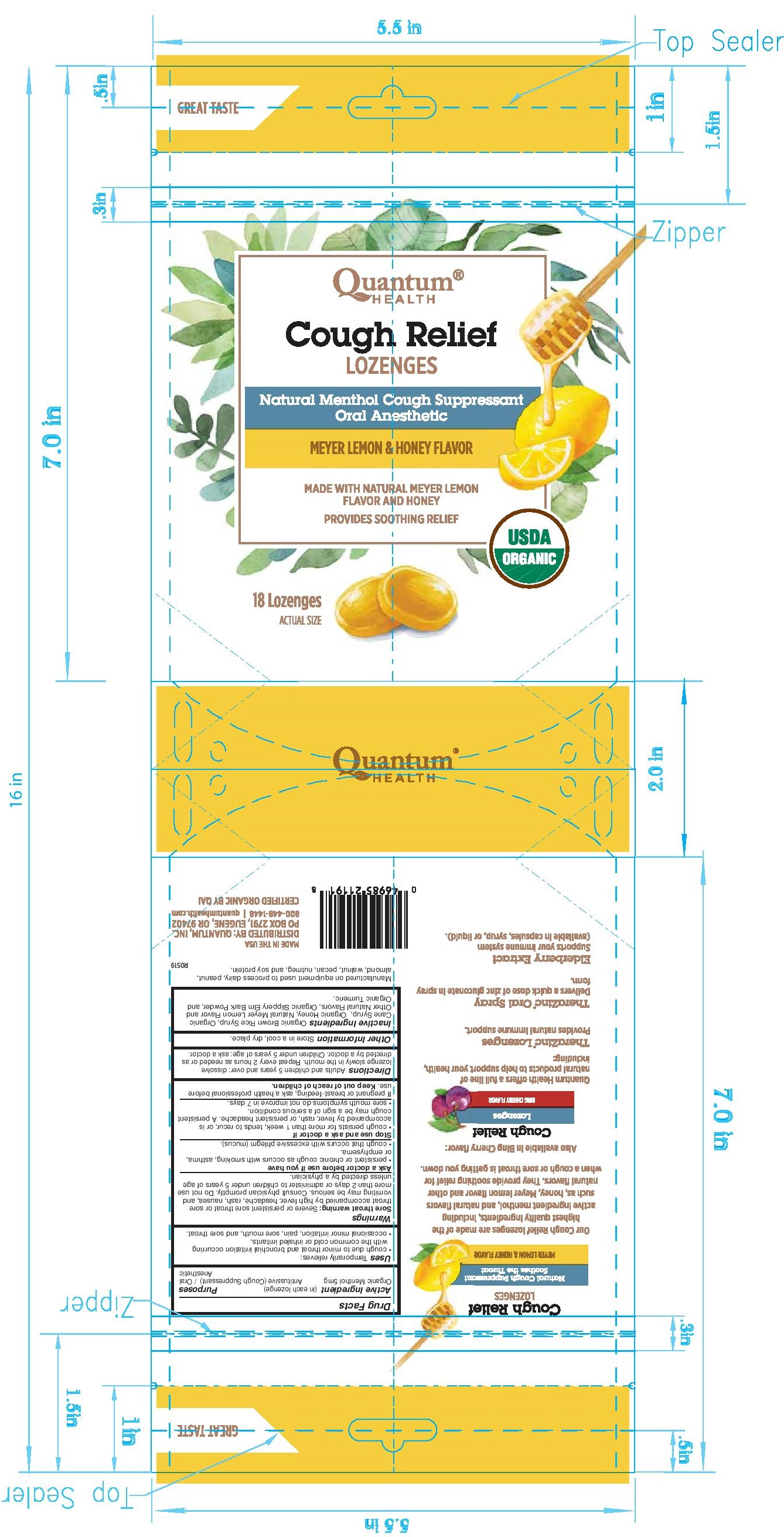 DRUG LABEL: Meyer Lemon and Honey-Cough Relief Lozenges (Oral Anesthetic)
NDC: 70084-614 | Form: LOZENGE
Manufacturer: Quantum, Inc.
Category: otc | Type: HUMAN OTC DRUG LABEL
Date: 20230110

ACTIVE INGREDIENTS: MENTHOL 5 mg/1 1
INACTIVE INGREDIENTS: MEYER LEMON; CURCUMA LONGA WHOLE; BARLEY MALT SYRUP; SUGARCANE; HONEY; ULMUS RUBRA BARK

Meyer Lemon and Honey-Cough Relief Lozenges (Oral Anesthetic)

ACTIVE INGREDIENT

(In each lozenge)

Organic Menthol 5mg

PURPOSE

Antitussive (Cough Suppressant) / Oral Anesthetic

WARNINGS

Sore Throat Warning: Severe or persistent sore throat or sore throat accompanied by high fever, headache, rash, nausea, and vomiting may be serious. Consult physician promptly. Do not use more than 2 days or administer to children under 5 years of age unless directed by a physician.

Ask a doctor before use if you have:

- persistent or chronic cough as occurs with smoking, asthma, or emphysema.

- cough that occurs with excessive phlegm (mucus).

STOP USE

- cough persists for more than 1 week, tends to recur, or is accompanied by fever, rash, or persistent headache. A persistent cough may be a sign of a serious condition.

- sore mouth symptoms do not improve in 7 days.

PREGNANCY OR BREAST FEEDING

If pregnant or breast-feeding, ask a health professional before use.

Keep out of reach of children.

DOSAGE AND ADMINISTRATION

Adults and children 5 years and over: dissolve lozenge slowly in the mouth. Repeat every 2 hours as needed or as directed by a doctor. Children under 5years of age: ask a doctor.

OTHER SAFETY INFORMATION

Store in a cool, dry place.

INACTIVE INGREDIENT

Organic Brown Rice Syrup, Organic Cane Syrup, Organic Honey, Natural Meyer Lemon Flavor and Other Natural Flavors, Organic Slippery Elm Bark Powder, and Organic Tumeric.

INDICATIONS AND USAGE

- cough due to minor throat and bronchial irritation occurring with the common cold and inhaled irritation,

- occasional minor irritation, pain, sore mouth, and sore throat.